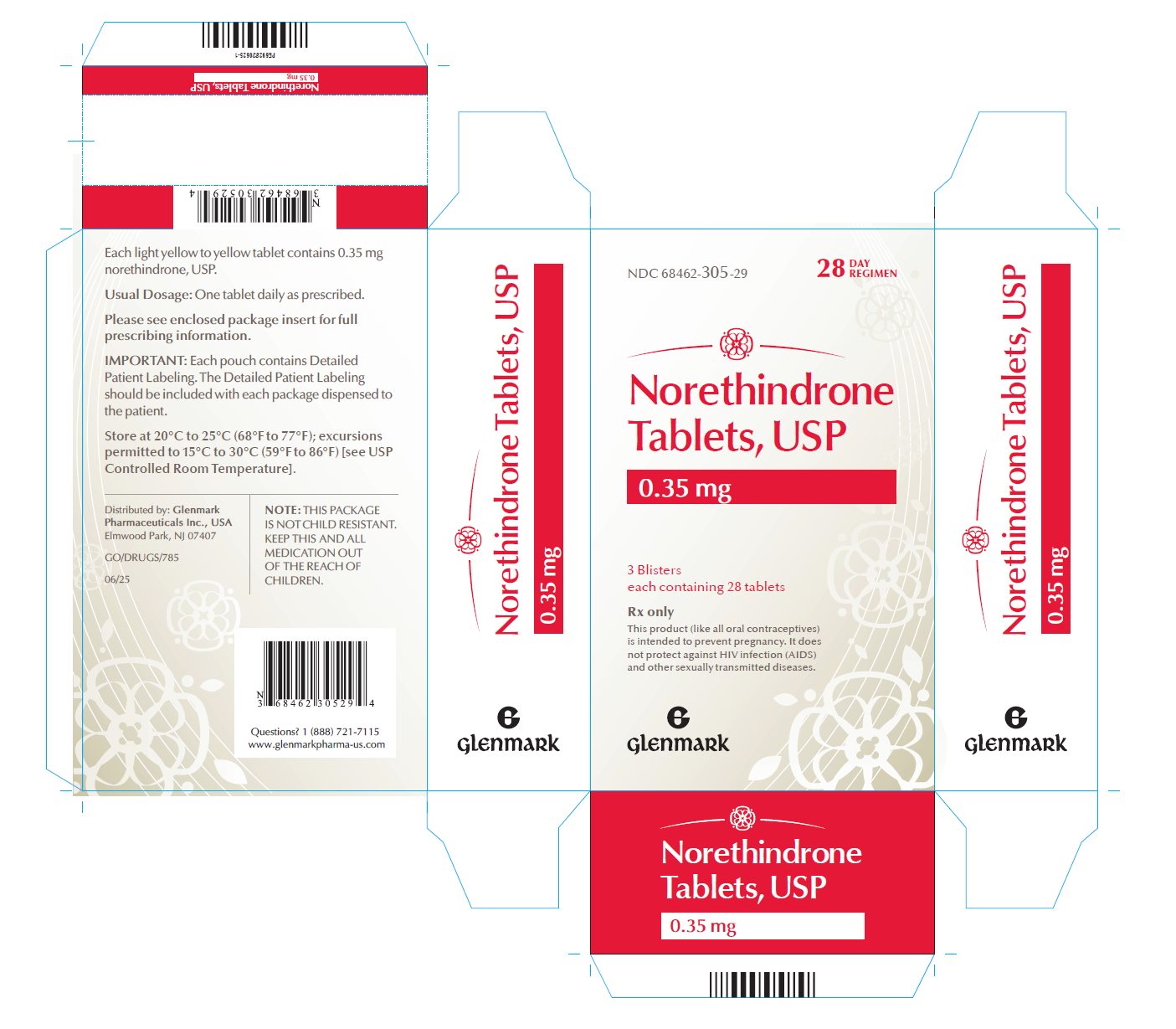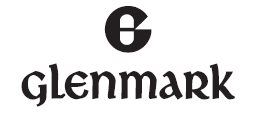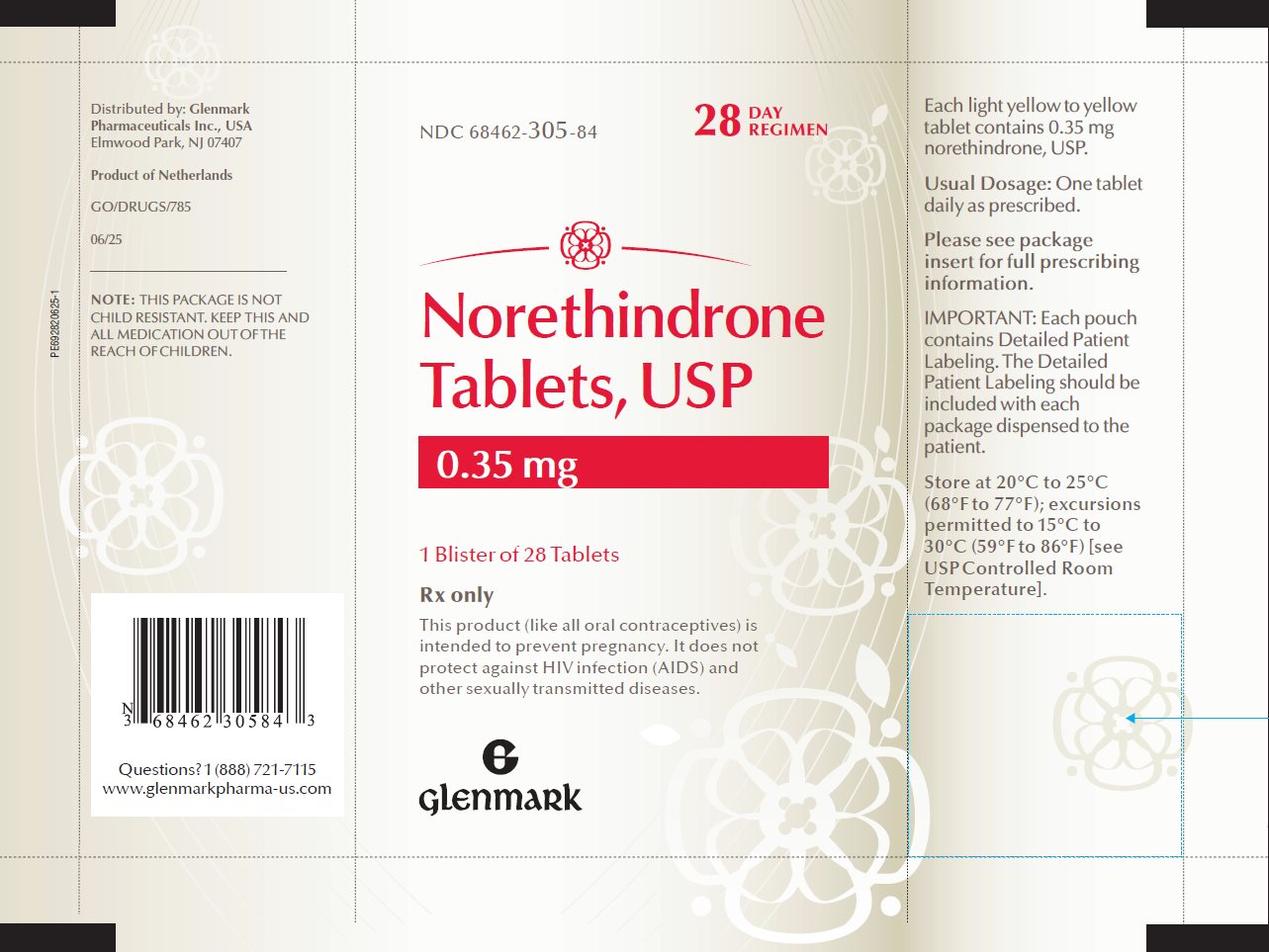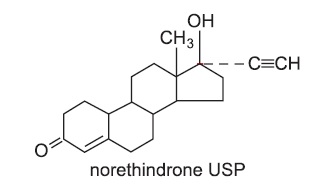 DRUG LABEL: Norethindrone
NDC: 68462-305 | Form: TABLET
Manufacturer: Glenmark Pharmaceuticals Inc., USA
Category: prescription | Type: HUMAN PRESCRIPTION DRUG LABEL
Date: 20260131

ACTIVE INGREDIENTS: NORETHINDRONE 0.35 mg/1 1
INACTIVE INGREDIENTS: SILICON DIOXIDE; STARCH, CORN; D&C YELLOW NO. 10; ETHYLCELLULOSE, UNSPECIFIED; ANHYDROUS LACTOSE; MAGNESIUM STEARATE; MICROCRYSTALLINE CELLULOSE; POVIDONE, UNSPECIFIED; TALC

Norethindrone Tablets, USP 0.35 mg

Patients should be counseled that this product does not protect against HIV infection (AIDS) and other sexually transmitted diseases.

DESCRIPTION

Each tablet contains 0.35 mg norethindrone, USP. Inactive ingredients include colloidal silicon dioxide, corn starch, D&C Yellow No. 10, ethyl cellulose, lactose anhydrous, magnesium stearate, microcrystalline cellulose, povidone, sodium starch glycolate, methylene chloride, isopropyl alcohol and talc.

CLINICAL PHARMACOLOGY

1. Mode of Action

Norethindrone progestin-only oral contraceptives prevent conception by suppressing ovulation in approximately half of users, thickening the cervical mucus to inhibit sperm penetration, lowering the midcycle LH and FSH peaks, slowing the movement of the ovum through the fallopian tubes and altering the endometrium.

2. Pharmacokinetics

Serum progestin levels peak about two hours after oral administration, followed by rapid distribution and elimination. By 24 hours after drug ingestion, serum levels are near baseline, making efficacy dependent upon rigid adherence to the dosing schedule. There are large variations in serum levels among individual users. Progestin-only administration results in lower steady-state serum progestin levels and a shorter elimination half-life than concomitant administration with estrogens.

INDICATIONS AND USAGE

1. Indications

Progestin-only oral contraceptives are indicated for the prevention of pregnancy.

2. Efficacy

If used perfectly, the first-year failure rate for progestin-only oral contraceptives is 0.3%. However, the typical failure rate is estimated to be closer to 9%, due to late or omitted pills. Table 1 lists the pregnancy rates for users of all major methods of contraception.

Table 1: Percentage of Women Experiencing an Unintended Pregnancy During the First Year of Typical Use and the First Year of Perfect Use of Contraception and the Percentage Continuing Use at the End of the First Year. United States.
 | % of Women Experiencing an Unintended Pregnancy within the First Year of Use |  | % of Women Continuing Use at One Year
Method; (1) | Typical Use; (2) | Perfect Use; (3) | (4)
No method^4 | 85 | 85
Spermicides | 28 | 18 | 42
Fertility awareness-based methods | 24 |  | 47
Standard Days method^6 |  | 5
TwoDay method^6 |  | 4
Ovulation method^6 |  | 3
Symptothermal method^6 |  | 0.4
Withdrawal | 22 | 4 | 46
Sponge |  |  | 36
Parous women | 24 | 20
Nulliparous women | 12 | 9
Condom^7
Female (fc) | 21 | 5 | 41
Male | 18 | 2 | 43
Diaphragm^8 | 12 | 6 | 57
Combined pill and progestin-only pill | 9 | 0.3 | 67
Norelgestromin and ethinyl estradiol patch | 9 | 0.3 | 67
NuvaRing | 9 | 0.3 | 67
Depo-Provera | 6 | 0.2 | 56
Intrauterine contraceptives
ParaGard (copper T) | 0.8 | 0.6 | 78
Mirena (LNg) | 0.2 | 0.2 | 80
Implanon | 0.05 | 0.05 | 84
Female sterilization | 0.5 | 0.5 | 100
Male sterilization | 0.15 | 0.10 | 100
Emergency Contraception: Emergency contraceptive pills or insertion of a copper intrauterine contraceptive after unprotected intercourse substantially reduces the risk of pregnancy.^9 (See Chapter 6.).
Lactational Amenorrhea Method: LAM is highly effective, temporary method of contraception
10 (See Chapter 18.).
Source: Trussell J. Contraceptive Efficacy. In Hatcher RA, Trussell J, Nelson AL, Cates W, Kowal D, Policar M. Contraceptive Techology: Twentieth Revised Edition. New York NY: Ardent Media, 2011.

Notes:

1. Among typical couples who initiate use of a method (not necessarily for the first time), the percentage who experience an accidental pregnancy during the first year if they do not stop use for any other reason. Estimates of the probability of pregnancy during the first year of typical use for spermicides, withdrawal, fertility awareness-based methods, the diaphragm, the male condom, the oral contraceptive pill, and Depo-Provera are taken from the 1995 National Survey of Family Growth corrected for underreporting of abortion; see the text for the derivation of estimates for the other methods.
2. Among couples who initiate use of a method (not necessarily for the first time) and who use it perfectly (both consistently and correctly), the percentage who experience an accidental pregnancy during the first year if they do not stop use for any other reason. See the text for the derivation of the estimate for each method.
3. Among couples attempting to avoid pregnancy, the percentage who continue to use a method for 1 year.
4. The percentages becoming pregnant in columns (2) and (3) are based on data from populations where contraception is not used and from women who cease using contraception in order to become pregnant. Among such populations, about 89% become pregnant within 1 year. This estimate was lowered slightly (to 85%) to represent the percentage who would become pregnant within 1 year among women now relying on reversible methods of contraception if they abandoned contraception altogether.
5. Foams, creams, gels, vaginal suppositories, and vaginal film.
6. The Ovulation and TwoDay methods are based on evaluation of cervical mucus. The Standard Days method avoids intercourse on cycle days 8 through 19. The Symptothermal method is a double-check method based on evaluation of cervical mucus to determine the first fertile day and evaluation of cervical mucus and temperature to determine the last fertile day.
7. Without spermicides.
8. With spermicidal cream or jelly.
9. ella, Plan B One-Step and Next Choice are the only dedicated products specifically marketed for
emergency contraception. The label for Plan B One-Step (one dose is 1 white pill) says to take the pill within 72 hours after unprotected intercourse. Research has shown that all of the brands listed here are effective when used within 120 hours after unprotected sex. The label for Next Choice (one dose is 1 peach pill) says to take 1 pill within 72 hours after unprotected intercourse and another pill 12 hours later. Research has shown that both pills can be taken at the same time with no decrease in efficacy or increase in side effects and that they are effective when used within 120 hours after unprotected sex. The FDA has in addition declared the following 19 brands of oral contraceptives to be safe and effective for emergency contraception: Ogestrel (1 dose is 2 white pills), Nordette (1 dose is 4 light-orange pills), Cryselle, Levora, Low-Ogestrel, Lo/Ovral, or Quasence (1 dose is 4 white pills), Jolessa, Portia, Seasonale or Trivora (1 dose is 4 pink pills), Seasonique (1 dose is 4 light-blue-green pills), Enpresse (one dose is 4 orange pills), Lessina (1 dose is 5 pink pills), Aviane or LoSeasonique (one dose is 5 orange pills), Lutera or Sronyx (one dose is 5 white pills), and Lybrel (one dose is 6 yellow pills).

Norethindrone tablets have not been studied for and are not indicated for use in emergency contraception.

CONTRAINDICATIONS

Progestin-only oral contraceptives (POPs) should not be used by women who currently have the following conditions:

- Known or suspected pregnancy
- Known or suspected carcinoma of the breast.
- Undiagnosed abnormal genital bleeding
- Hypersensitivity to any component of this product
- Benign or malignant liver tumors
- Acute liver disease

WARNINGS

Cigarette smoking increases the risk of serious cardiovascular disease. Women who use oral contraceptives should be strongly advised not to smoke.

Norethindrone tablets do not contain estrogen and, therefore, this insert does not discuss the serious health risks that have been associated with the estrogen component of combined oral contraceptives (COCs). The healthcare professional is referred to the prescribing information of combined oral contraceptives for a discussion of those risks. The relationship between progestin-only oral contraceptives and these risks is not fully defined. The healthcare professional should remain alert to the earliest manifestation of symptoms of any serious disease and discontinue oral contraceptive therapy when appropriate.

1. Ectopic Pregnancy

The incidence of ectopic pregnancies for progestin-only oral contraceptive users is 5 per 1000 woman-years. Up to 10% of pregnancies reported in clinical studies of progestin-only oral contraceptive users are extrauterine. Although symptoms of ectopic pregnancy should be watched for, a history of ectopic pregnancy need not be considered a contraindication to use of this contraceptive method. Healthcare professionals should be alert to the possibility of an ectopic pregnancy in women who become pregnant or complain of lower abdominal pain while on progestin-only oral contraceptives.

2. Delayed Follicular Atresia/Ovarian Cysts

If follicular development occurs, atresia of the follicle is sometimes delayed and the follicle may continue to grow beyond the size it would attain in a normal cycle. Generally these enlarged follicles disappear spontaneously. Often they are asymptomatic; in some cases they are associated with mild abdominal pain. Rarely they may twist or rupture, requiring surgical intervention.

3. Irregular Genital Bleeding

Irregular menstrual patterns are common among women using progestin-only oral contraceptives. If genital bleeding is suggestive of infection, malignancy or other abnormal conditions, such nonpharmacologic causes should be ruled out. If prolonged amenorrhea occurs, the possibility of pregnancy should be evaluated.

4. Carcinoma of the Breast and Reproductive Organs

Some epidemiological studies of oral contraceptive users have reported an increased relative risk of developing breast cancer, particularly at a younger age and apparently related to duration of use. These studies have predominantly involved combined oral contraceptives and there is insufficient data to determine whether the use of POPs similarly increases the risk.

A meta-analysis of 54 studies found a small increase in the frequency of having breast cancer diagnosed for women who were currently using combined oral contraceptives or had used them within the past ten years.

This increase in the frequency of breast cancer diagnosis, within ten years of stopping use, was generally accounted for by cancers localized to the breast. There was no increase in the frequency of having breast cancer diagnosed ten or more years after cessation of use.

Women with breast cancer should not use oral contraceptives because the role of female hormones in breast cancer has not been fully determined.

Some studies suggest that oral contraceptive use has been associated with an increase in the risk of cervical intraepithelial neoplasia in some populations of women. However, there continues to be controversy about the extent to which such findings may be due to differences in sexual behavior and other factors. There is insufficient data to determine whether the use of POPs increases the risk of developing cervical intraepithelial neoplasia.

5. Hepatic Neoplasia

Benign hepatic adenomas are associated with combined oral contraceptive use, although the incidence of benign tumors is rare in the United States. Rupture of benign, hepatic adenomas may cause death through intra-abdominal hemorrhage.

Studies have shown an increased risk of developing hepatocellular carcinoma in combined oral contraceptive users. However, these cancers are rare in the U.S. There is insufficient data to determine whether POPs increase the risk of developing hepatic neoplasia.

PRECAUTIONS

1. General

Patients should be counseled that this product does not protect against HIV infection (AIDS) and other sexually transmitted diseases.

2. Physical Examination and Follow up

It is considered good medical practice for sexually active women using oral contraceptives to have annual history and physical examinations. The physical examination may be deferred until after initiation of oral contraceptives if requested by the woman and judged appropriate by the healthcare professional.

3. Carbohydrate and Lipid Metabolism

Some users may experience slight deterioration in glucose tolerance, with increases in plasma insulin but women with diabetes mellitus who use progestin-only oral contraceptives do not generally experience changes in their insulin requirements. Nonetheless, prediabetic and diabetic women in particular should be carefully monitored while taking POPs.

Lipid metabolism is occasionally affected in that HDL, HDL2, and apolipoprotein A-I and A-II may be decreased; hepatic lipase may be increased. There is usually no effect on total cholesterol, HDL3, LDL, or VLDL.

4. Drug Interactions

Consult the labeling of concurrently-used drugs to obtain further information about interactions with hormonal contraceptives or the potential for enzyme alterations.

- Effects of Other Drugs on Hormonal Contraceptives

Substances decreasing the systemic concentrations of hormonal contraceptives (HCs) and potentially diminishing the efficacy of HCs:

Drugs or herbal products that induce certain enzymes, including cytochrome P450 3A4 (CYP3A4), may decrease the systemic concentrations of HCs and potentially diminish the effectiveness of HCs or increase breakthrough bleeding.

Some drugs or herbal products that may decrease the effectiveness of HCs include efavirenz, phenytoin, barbiturates, carbamazepine, bosentan, felbamate, griseofulvin, oxcarbazepine, rifampicin, rifabutin, rufinamide, aprepitant, and products containing St. John’s wort. Interactions between HCs and other drugs may lead to breakthrough bleeding and/or contraceptive failure. Counsel women to use an alternative non-hormonal method of contraception or a back-up method when enzyme inducers are used with HCs, and to continue back-up non-hormonal contraception for 28 days after discontinuing the enzyme inducer to ensure contraceptive reliability.

Substances increasing the systemic concentrations of HCs:

Co-administration of certain HCs and strong or moderate CYP3A4 inhibitors such as itraconazole, voriconazole, fluconazole, grapefruit juice, or ketoconazole may increase the systemic concentrations of progestins, including norethindrone.

Human Immunodeficiency Virus (HIV)/Hepatitis C Virus (HCV) protease inhibitors and nonnucleoside reverse transcriptase inhibitors:

Significant decreases in systemic concentrations of progestin have been noted in cases of co-administration with some HIV protease inhibitors (e.g., nelfinavir, ritonavir, darunavir/ritonavir, (fos)amprenavir/ritonavir, lopinavir/ritonavir, and tipranavir/ritonavir), some HCV protease inhibitors (e.g., boceprevir and telaprevir), and some non-nucleoside reverse transcriptase inhibitors (e.g., nevirapine, efavirenz).

In contrast, significant increases in systemic exposure of the progestin have been noted in cases of co-administration with certain other HIV protease inhibitors (e.g., indinavir and atazanavir/ritonavir) and with other non-nucleoside reverse transcriptase inhibitors (e.g., etravirine).

These changes may be clinically relevant in some cases.

Consult the prescribing information of anti-viral and anti-retroviral concomitant medications to identify potential interactions.

- Effects of Hormonal Contraceptives on Other Drugs

Hormonal contraceptives may affect the metabolism of other drugs. Consequently, systemic concentrations may either increase (for example, cyclosporine) or decrease. Consult the labeling of all concurrently-used drugs to obtain further information about interactions with hormonal contraceptives or the potential for enzyme alterations.

- Interactions between ulipristal and hormonal contraceptives

Effectiveness of progestin-containing hormonal contraceptives and emergency contraceptive ulipristal acetate may be decreased if progestin-containing hormonal contraceptives are used within five days after ulipristal acetate dosing. Therefore, if a woman wishes to use norethindrone tablets after using ulipristal acetate, she should do so no sooner than 5 days after the intake of ulipristal acetate and she should use a reliable barrier method for subsequent acts of intercourse until her next menstrual period.

5. Interactions with Laboratory Tests

The following endocrine tests may be affected by progestin-only oral contraceptive use:

- Sex hormone-binding globulin (SHBG) concentrations may be decreased.
- Thyroxine concentrations may be decreased, due to a decrease in thyroid binding globulin (TBG).

6. Carcinogenesis

See WARNINGS.

7. Pregnancy

Many studies have found no effects on fetal development associated with long-term use of contraceptive doses of oral progestins. The few studies of infant growth and development that have been conducted have not demonstrated significant adverse effects. It is nonetheless prudent to rule out suspected pregnancy before initiating any hormonal contraceptive use.

8. Nursing Mothers

In general, no adverse effects have been found on breastfeeding performance or on the health, growth, or development of the infant. However, isolated post-marketing cases of decreased milk production have been reported. Small amounts of progestins pass into the breast milk of nursing mothers, resulting in detectable steroid levels in infant plasma.

9. Pediatric Use

Safety and efficacy of norethindrone tablets have been established in women of reproductive age. Safety and efficacy are expected to be the same for postpubertal adolescents under the age of 16 and for users 16 years and older. Use of this product before menarche is not indicated.

10. Fertility Following Discontinuation

The limited available data indicate a rapid return of normal ovulation and fertility following discontinuation of progestin-only oral contraceptives.

11. Headache

The onset or exacerbation of migraine or development of severe headache with focal neurological symptoms which is recurrent or persistent requires discontinuation of progestin-only contraceptives and evaluation of the cause.

INFORMATION FOR THE PATIENT

- See “Detailed Patient Labeling” for detailed information.
- Counseling issues

The following points should be discussed with prospective users before prescribing progestin-only oral contraceptives:

- The necessity of taking pills at the same time every day, including throughout all bleeding episodes.
- The need to use a backup method such as a condom and spermicide for the next 48 hours whenever a progestin-only oral contraceptive is taken 3 or more hours late.
- The potential side effects of progestin-only oral contraceptives, particularly menstrual irregularities.
- The need to inform the healthcare professional of prolonged episodes of bleeding, amenorrhea or severe abdominal pain.
- The importance of using a barrier method in addition to progestin-only oral contraceptives if a woman is at risk of contracting or transmitting STDs/HIV.

ADVERSE REACTIONS

Adverse reactions reported with the use of POPs include:

- Menstrual irregularity is the most frequently reported side effect.
- Frequent and irregular bleeding are common, while long duration of bleeding episodes and amenorrhea are less likely.
- Headache, breast tenderness, nausea, and dizziness are increased among progestin-only oral contraceptive users in some studies.
- Androgenic side effects such as acne, hirsutism, and weight gain occur rarely.

The following adverse reactions were also reported in clinical trials or during post-marketing experience: Gastrointestinal Disorders: vomiting, abdominal pain; General Disorders and Administration Site Conditions: fatigue, edema; Psychiatric Disorders: depression, nervousness; Musculoskeletal and Connective Tissue Disorders: pain in extremity; Reproductive System and Breast Disorders: genital discharge; breast pain, menstruation delayed, suppressed lactation, vaginal hemorrhage, menorrhagia, withdrawal bleed when product is stopped; Immune System Disorders: anaphylactic/anaphylactoid reaction, hypersensitivity; Hepatobiliary Disorders: hepatitis, jaundice cholestatic; Skin and Subcutaneous Tissue Disorders: alopecia, rash, rash pruritic.

OVERDOSAGE

There have been no reports of serious ill effects from overdosage, including ingestion by children.

DOSAGE AND ADMINISTRATION

To achieve maximum contraceptive effectiveness, norethindrone tablets must be taken exactly as directed. One tablet is taken every day, at the same time. Administration is continuous, with no interruption between pill packs. See Detailed Patient Labeling for detailed instruction.

HOW SUPPLIED

Norethindrone tablets, USP 0.35 mg are available in cartons (NDC 68462-305-29) of 3 blisters (NDC 68462-305-84), each containing 28 light yellow to yellow round, flat faced, bevelled edged, uncoated tablets with ‘305’ debossed on one side and ‘G’ on the other side.

STORAGE AND HANDLING

STORAGE: Store at 20°C to 25°C (68°F to 77°F); excursions permitted to 15°C to 30°C (59°F to 86°F) [see USP Controlled Room Temperature].

Keep out of reach of children.

REFERENCES

1. McCann M, and Potter L. Progestin-Only Oral Contraceptives: A Comprehensive Review. Contraception, 50:60 (Suppl. 1), December 1994.
2. Van Giersbergen PLM, Halabi A, Dingemanse J. Pharmacokinetic interaction between bosentan and the oral contraceptives norethisterone and ethinyl estradiol. Int J Clin Pharmacol Ther 2006;44(3):113-118.
3. Truitt ST, Fraser A, Gallo ME, Lopez LM, Grimes DA and Schulz KF. Combined hormonal versus nonhormonal versus progestin-only contraception in lactation (Review). The Cochrane Collaboration. 2007, Issue 3.
4. Halderman, LD and Nelson AL. Impact of early postpartum administration of progestin-only hormonal contraceptives compared with nonhormonal contraceptives on short-term breast feeding patterns. Am J Obstet Gynecol.; 186 (6): 1250-1258.
5. Ostrea EM, Mantaring III JB, Silvestre MA. Drugs that affect the fetus and newborn infant via the placenta or breast milk. Pediatr Clin N Am; 51 (2004): 539-579.
6. Cooke ID, Back DJ, Shroff NE: Norethisterone concentration in breast milk and infant and maternal plasma during ethynodiol diactetate administration. Contraception 1985; 31:611-21.
7. 2008 USPC Official:12/1/08-4/30/09, USP Monographs: Norethindrone Tablets (page 1 of 5)

Distributed by:

Glenmark Pharmaceuticals Inc., USA
Elmwood Park, NJ 07407

Questions? 1 (888) 721-7115
www.glenmarkpharma-us.com

July 2025

DETAILED PATIENT LABELING

Norethindrone Tablets, USP 0.35 mg

This product (like all oral contraceptives) is used to prevent pregnancy. It does not protect against HIV infection (AIDS) or other sexually transmitted diseases.

DESCRIPTION

Norethindrone tablets, USP 0.35 mg

Each tablet contains 0.35 mg norethindrone USP. Inactive ingredients include colloidal silicon dioxide, corn starch, D&C Yellow No. 10, ethyl cellulose, lactose anhydrous, magnesium stearate, microcrystalline cellulose, povidone, sodium starch glycolate, methylene chloride, isopropyl alcohol and talc.

INTRODUCTION

This leaflet is about birth control pills that contain one hormone, a progestin. Please read this leaflet before you begin to take your pills. It is meant to be used along with talking with your healthcare professional.

Progestin-only pills are often called “POPs” or “the minipill”. POPs have less progestin than the combined birth control pill (or “the pill”) which contains both an estrogen and a progestin.

HOW EFFECTIVE ARE POPs?

About 1 in 200 POP users will get pregnant in the first year if they all take POPs perfectly (that is, on time, every day). About 1 in 20 “typical” POP users (including women who are late taking pills or miss pills) gets pregnant in the first year of use. Table 2 will help you compare the efficacy of different methods.

Table 2: Percentage of Women Experiencing an Unintended Pregnancy During the First Year of Typical Use and the First Year of Perfect Use of Contraception and the Percentage Continuing Use at the End of the First Year. United States.
 | % of Women Experiencing an Unintended Pregnancy within the First Year of Use |  | % of Women Continuing Use at One Year
Method; (1) | Typical Use; (2) | Perfect Use; (3) | (4)
No method^4 | 85 | 85
Spermicides | 28 | 18 | 42
Fertility awareness-based methods | 24 |  | 47
Standard Days method^6 |  | 5
TwoDay method^6 |  | 4
Ovulation method^6 |  | 3
Symptothermal method^6 |  | 0.4
Withdrawal | 22 | 4 | 46
Sponge |  |  | 36
Parous women | 24 | 20
Nulliparous women | 12 | 9
Condom^7
Female (fc) | 21 | 5 | 41
Male | 18 | 2 | 43
Diaphragm^8 | 12 | 6 | 57
Combined pill and progestin-only pill | 9 | 0.3 | 67
Norelgestromin and ethinyl estradiol patch | 9 | 0.3 | 67
NuvaRing | 9 | 0.3 | 67
Depo-Provera | 6 | 0.2 | 56
Intrauterine contraceptives
ParaGard (copper T) | 0.8 | 0.6 | 78
Mirena (LNg) | 0.2 | 0.2 | 80
Implanon | 0.05 | 0.05 | 84
Female sterilization | 0.5 | 0.5 | 100
Male sterilization | 0.15 | 0.10 | 100

Emergency Contraception: Emergency contraceptive pills or insertion of a copper intrauterine contraceptive after unprotected intercourse substantially reduces the risk of pregnancy.^9 (See Chapter 6.).

Lactational Amenorrhea Method: LAM is a highly effective, temporary method of contraception.10 (See Chapter 18.)

Source: Trussell J. Contraceptive Efficacy. In Hatcher RA, Trussell J, Nelson AL, Cates W, Kowal D, Policar M. Contraceptive Techology: Twentieth Revised Edition. New York NY: Ardent Media, 2011.

Notes:

1. Among typical couples who initiate use of a method (not necessarily for the first time), the percentage who experience an accidental pregnancy during the first year if they do not stop use for any other reason. Estimates of the probability of pregnancy during the first year of typical use for spermicides, withdrawal, fertility awareness-based methods, the diaphragm, the male condom, the oral contraceptive pill, and Depo-Provera are taken from the 1995 National Survey of Family Growth corrected for underreporting of abortion; see the text for the derivation of estimates for the other methods.
2. Among couples who initiate use of a method (not necessarily for the first time) and who use it perfectly (both consistently and correctly), the percentage who experience an accidental pregnancy during the first year if they do not stop use for any other reason. See the text for the derivation of the estimate for each method.
3. Among couples attempting to avoid pregnancy, the percentage who continue to use a method for 1 year.
4. The percentages becoming pregnant in columns (2) and (3) are based on data from populations where contraception is not used and from women who cease using contraception in order to become pregnant. Among such populations, about 89% become pregnant within 1 year. This estimate was lowered slightly (to 85%) to represent the percentage who would become pregnant within 1 year among women now relying on reversible methods of contraception if they abandoned contraception altogether.
5. Foams, creams, gels, vaginal suppositories, and vaginal film.
6. The Ovulation and TwoDay methods are based on evaluation of cervical mucus. The Standard Days method avoids intercourse on cycle days 8 through 19. The Symptothermal method is a double-check method based on evaluation of cervical mucus to determine the first fertile day and evaluation of cervical mucus and temperature to determine the last fertile day.
7. Without spermicides.
8. With spermicidal cream or jelly.
9. ella, Plan B One-Step and Next Choice are the only dedicated products specifically marketed for emergency contraception. The label for Plan B One-Step (one dose is 1 white pill) says to take the pill within 72 hours after unprotected intercourse. Research has shown that all of the brands listed here are effective when used within 120 hours after unprotected sex. The label for Next Choice (one dose is 1 peach pill) says to take 1 pill within 72 hours after unprotected intercourse and another pill 12 hours later. Research has shown that both pills can be taken at the same time with no decrease in efficacy or increase in side effects and that they are effective when used within 120 hours after unprotected sex. The FDA has in addition declared the following 19 brands of oral contraceptives to be safe and effective for emergency contraception: Ogestrel (1 dose is 2 white pills), Nordette (1 dose is 4 light-orange pills), Cryselle, Levora, Low-Ogestrel, Lo/Ovral, or Quasence (1 dose is 4 white pills), Jolessa, Portia, Seasonale or Trivora (1 dose is 4 pink pills), Seasonique (1 dose is 4 light-blue-green pills), Enpresse (one dose is 4 orange pills), Lessina (1 dose is 5 pink pills), Aviane or LoSeasonique (one dose is 5 orange pills), Lutera or Sronyx (one dose is 5 white pills), and Lybrel (one dose is 6 yellow pills).
10. However, to maintain effective protection against pregnancy, another method of contraception must be used as soon as menstruation resumes, the frequency or duration of breastfeeds is reduced, bottle feeds are introduced, or the baby reaches 6 months of age.

Norethindrone tablets have not been studied for and are not indicated for use in emergency contraception.

HOW DO POPs WORK?

POPs can prevent pregnancy in different ways including:

- They make the cervical mucus at the entrance to the womb (the uterus) too thick for the sperm to get through to the egg
- They prevent ovulation (release of the egg from the ovary) in about half of the cycles
- They also affect other hormones, the fallopian tubes and the lining of the uterus

YOU SHOULD NOT TAKE POPs

- If there is any chance you may be pregnant.
- If you have breast cancer
- If you have bleeding between your periods that has not been diagnosed
- If you are hypersensitive, or allergic, to any component of this product.
- If you have liver tumors, either benign or cancerous.
- If you have acute liver disease.

RISKS OF TAKING POPs

Cigarette smoking greatly increases the possibility of suffering heart attacks and strokes. Women who use oral contraceptives are strongly advised not to smoke.

WARNING:

If you have sudden or severe pain in your lower abdomen or stomach area, you may have an ectopic pregnancy or an ovarian cyst. If this happens, you should contact your healthcare professional immediately.

Ectopic Pregnancy

An ectopic pregnancy is a pregnancy outside the womb. Because POPs protect against pregnancy, the chance of having a pregnancy outside the womb is very low. If you do get pregnant while taking POPs, you have a slightly higher chance that the pregnancy will be ectopic than do users of some other birth control methods.

Ovarian Cysts

These cysts are small sacs of fluid in the ovary. They are more common among POP users than among users of most other birth control methods. They usually disappear without treatment and rarely cause problems.

Cancer of the Reproductive Organs and Breasts

Some studies in women who use combined oral contraceptives that contain both estrogen and a progestin have reported an increase in the risk of developing breast cancer, particularly at a younger age and apparently related to duration of use. There is insufficient data to determine whether the use of POPs similarly increases this risk.

A meta-analysis of 54 studies found a small increase in the frequency of having breast cancer diagnosed for women who were currently using combined oral contraceptives or had used them within the past ten years. This increase in the frequency of breast cancer diagnosis, within ten years of stopping use, was generally accounted for by cancers localized to the breast. There was no increase in the frequency of having breast cancer diagnosed ten or more years after cessation of use.

Some studies have found an increase in the incidence of cancer of the cervix in women who use oral contraceptives. However, this finding may be related to factors other than the use of oral contraceptives and there is insufficient data to determine whether the use of POPs increases the risk of developing cancer of the cervix.

Liver Tumors

In rare cases, combined oral contraceptives can cause benign but dangerous liver tumors. These benign liver tumors can rupture and cause fatal internal bleeding. In addition, some studies report an increased risk of developing liver cancer among women who use combined oral contraceptives. However, liver cancers are rare. There is insufficient data to determine whether POPs increase the risk of liver tumors.

Diabetic Women

Diabetic women taking POPs do not generally require changes in the amount of insulin they are taking. However, your healthcare professional may monitor you more closely under these conditions.

SEXUALLY TRANSMITTED DISEASES (STDs)

WARNING: POPs do not protect against getting or giving someone HIV (AIDS) or any other STD, such as chlamydia, gonorrhea, genital warts or herpes

SIDE EFFECTS

Irregular Bleeding:

The most common side effect of POPs is a change in menstrual bleeding. Your periods may be either early or late, and you may have some spotting between periods. Taking your pills late or missing pills can result in some spotting or bleeding.

Other Side Effects

Less common side effects include headaches, tender breasts, nausea, vomiting, dizziness, and fatigue. Depression, nervousness, leg pain, vaginal discharge, fluid retention, allergic reactions, jaundice or a yellowing of the skin or eyeballs, loss of scalp hair, rash/itchy rash, weight gain, acne and extra hair on your face and body have been reported, but are rare.

If you are concerned about any of these side effects, check with your healthcare professional.

USING POPs WITH OTHER MEDICINES

Before taking a POP, inform your healthcare professional of any other medication, including over-the-counter medicine, that you may be taking.

These medicines can make POPs less effective:

Medicines for seizures such as:

- Phenytoin
- Carbamazepine
- Phenobarbital
- Felbamate
- Oxcarbazepine
- Rufinamide

Medicine for nausea and vomiting caused by certain anti-cancer (chemotherapy) medicines:

- (Fos)aprepitant

Medicines for tuberculosis (TB):

- Rifampin and rifabutin

Medicine for fungal infections such as:

- Griseofulvin

Medicine for pulmonary hypertension such as:

- Bosentan

Medicines used for the treatment of HIV infections or AIDS and infections due to Hepatitis C such as:

- Efavirenz, nevirapine, nelfinavir, and some ritonavir-containing drugs

Herbal products such as:

- St. John’s wort

These medicines and substances can increase your exposure to POPs:

Grapefruit juice

Medicines for fungal infections such as:

- Itraconazole
- Voriconazole
- Fluconazole
- Ketoconazole

Before you begin taking any new medicines be sure your healthcare professional knows you are taking a progestin-only birth control pill.

HOW TO TAKE POPs

IMPORTANT POINTS TO REMEMBER

- POPs must be taken at the same time every day, so choose a time and then take the pill at that same time every day. Every time you take a pill late, and especially if you miss a pill, you are more likely to get pregnant.
- Start the next pack the day after the last pack is finished. There is no break between packs. Always have your next pack of pills ready.
- You may have some menstrual spotting between periods. Do not stop taking your pills if this happens.
- If you vomit soon after taking a pill, use a backup method (such as a condom and/or a spermicide) for 48 hours.
- If you want to stop taking POPs, you can do so at any time, but, if you remain sexually active and don’t wish to become pregnant, be certain to use another birth control method.
- If you are not sure about how to take POPs, ask your healthcare professional.

STARTING POPs

- It’s best to take your first POP on the first day of your menstrual period.
- If you decide to take your first POP on another day, use a backup method (such as a condom and/or a spermicide) every time you have sex during the next 48 hours.
- If you have had a miscarriage or an abortion, you can start POPs the next day.

IF YOU ARE LATE OR MISS TAKING YOUR POPs

- If you are more than 3 hours late or you miss one or more POPs:
- TAKE a missed pill as soon as you remember that you missed it,
- THEN go back to taking POPs at your regular time,
- BUT be sure to use a backup method (such as a condom and/or a spermicide) every time you have sex for the next 48 hours.
- If you are not sure what to do about the pills you have missed, keep taking POPs and use a backup method until you can talk to your healthcare professional.

IF YOU ARE BREASTFEEDING

- If you are fully breastfeeding (not giving your baby any food or formula), you may start your pills 6 weeks after delivery.
- If you are partially breastfeeding (giving your baby some food or formula), you should start taking pills by 3 weeks after delivery.

IF YOU ARE SWITCHING PILLS

- If you are switching from the combined pills to POPs, take the first POP the day after you finish the last active combined pill. Do not take any of the 7 inactive pills from the combined pill pack. You should know that many women have irregular periods after switching to POPs, but this is normal and to be expected.
- If you are switching from POPs to the combined pills, take the first active combined pill on the first day of your period, even if your POPs pack is not finished.
- If you switch to another brand of POPs, start the new brand anytime.
- If you are breastfeeding, you can switch to another method of birth control at any time, except do not switch to the combined pills until you stop breastfeeding or at least until 6 months after delivery.

PREGNANCY WHILE ON THE PILL

If you think you are pregnant, contact your healthcare professional. Even though research has shown that POPs do not cause harm to the unborn baby, it is always best not to take any drugs or medicines that you don’t need when you are pregnant.

You should get a pregnancy test:

- If your period is late and you took one or more pills late or missed taking them and had sex without a backup method.
- Anytime it has been more than 45 days since the beginning of your last period.

WILL POPs AFFECT YOUR ABILITY TO GET PREGNANT LATER?

If you want to become pregnant, simply stop taking POPs. POPs will not delay your ability to get pregnant.

BREASTFEEDING

If you are breastfeeding, POPs will not affect the quality or amount of your breast milk or the health of your nursing baby. However, isolated cases of decreased milk production have been reported.

OVERDOSE

No serious problems have been reported when many pills were taken by accident, even by a small child, so there is usually no reason to treat an overdose.

OTHER QUESTIONS OR CONCERNS

If you have any questions or concerns, check with your healthcare professional. You can also ask for the more detailed “Professional Labeling” written for doctors and other healthcare professionals.

HOW TO STORE YOUR POPs

Store at 20°C to 25°C (68°F to 77°F); excursions permitted to 15°C to 30°C (59°F to 86°F) [see USP Controlled Room Temperature].

Keep out of reach of children.

Distributed by:

Glenmark Pharmaceuticals Inc., USA
Elmwood Park, NJ 07407

Questions? 1 (888) 721-7115
www.glenmarkpharma-us.com

July 2025